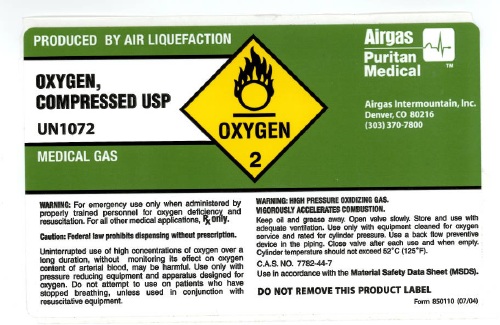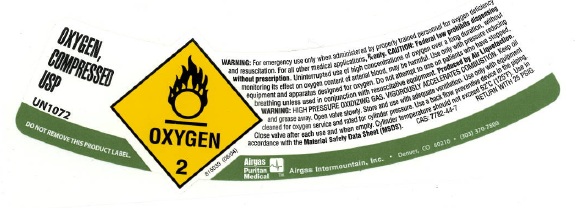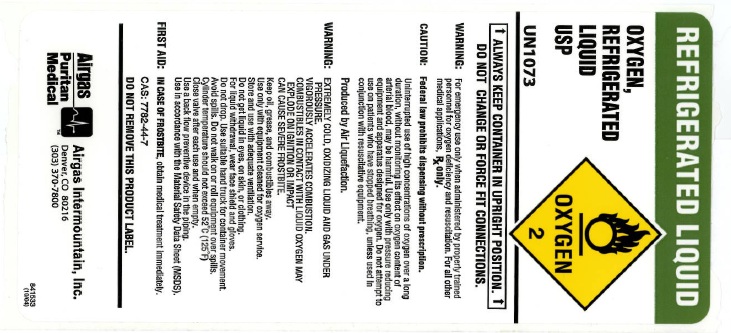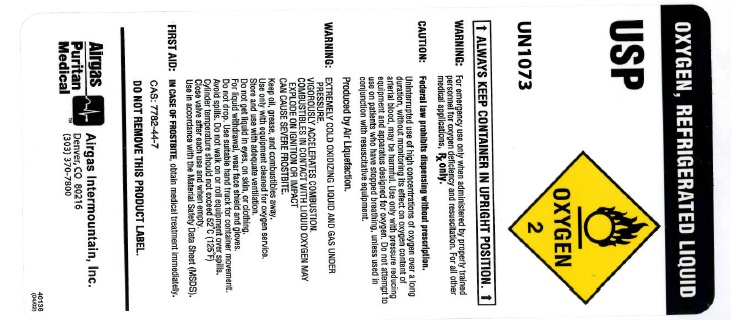 DRUG LABEL: Oxygen
NDC: 58420-001 | Form: GAS
Manufacturer: Airgas Intermountain Inc
Category: prescription | Type: HUMAN PRESCRIPTION DRUG LABEL
Date: 20110222

ACTIVE INGREDIENTS: Oxygen 992 mL/1 L

oxygen

PACKAGE LABEL

PRODUCED BY AIR LIQUEFACTION
OXYGEN, COMPRESSED LIQUID USP UN1072 MEDICAL GAS OXYGEN 2
AIRGAS PURITAN MEDICAL Airgas Intermountain, Inc. Denver, CO 80216 (303) 370-7800
WARNING: For emergency use only when administered by properly trained personnel for oxygen deficiency and resuscitation. For all other medical applications, Rx only.
CAUTION: Federal law prohibits dispensing without prescription. Uninterrupted use of high concentrations of oxygen over a long duration, without monitoring its effect on oxygen content of arterial blood, may be harmful. Use only with pressure reducing equipment and apparatus designed for oxygen. Do not attempt to use on patients who have stopped breathing, unless used in conjunction with resuscitative equipment.
WARNING: HIGH PRESSURE OXIDIZING GAS. VIGOROUSLY ACCELERATES COMBUSTION. Keep oil, grease away. Open valve slowly. Store and use with adequate ventilation. Use only with equipment cleaned for oxygen service and rated for cylinder pressure. Use back flow preventive device in the piping. Close valve after each use and when empty. Cylinder temperature should not exceed 52C (125F). C.A.S. NO. 7782-44-7 Use in accordance with the Material Safety Data Sheets (MSDS). DO NOT REMOVE THIS PRODUCT LABEL
Form 850110 (07/04)

PACKAGE LABEL

OXYGEN, COMPRESSED LIQUID USP UN1072 DO NOT REMOVE THIS PRODUCT LABEL OXYGEN 2 816033 (08/04)
WARNING: For emergency use only when administered by properly trained personnel for oxygen deficiency and resuscitation. For all other medical applications, Rx only.
CAUTION: Federal law prohibits dispensing without prescription. Uninterrupted use of high concentrations of oxygen over a long duration, without monitoring its effect on oxygen content of arterial blood, may be harmful. Use only with pressure reducing equipment and apparatus designed for oxygen. Do not attempt to use on patients who have stopped breathing, unless used in conjunction with resuscitative equipment. Produced by Air Liquefaction.
WARNING: HIGH PRESSURE OXIDIZING GAS. VIGOROUSLY ACCELERATES COMBUSTION. Keep oil, grease away. Open valve slowly. Store and use with adequate ventilation. Use only with equipment cleaned for oxygen service and rated for cylinder pressure. Use back flow preventive device in the piping. Close valve after each use and when empty. Cylinder temperature should not exceed 52C (125F). Use in accordance with the Material Safety Data Sheets (MSDS). CAS: 7782-44-7 RETURN WITH 25 PSIG
AIRGAS PURITAN MEDICAL Airgas Intermountain, Inc. Denver, CO 80216 (303) 370-7800

PACKAGE LABEL

REFRIGERATED LIQUID
OXYGEN, REFRIGERATED LIQUID USP UN1073 OXYGEN 2
ALWAYS KEEP CONTAINER IN UPRIGHT POSITION DO NOT CHANGE OR FORCEFIT CONNECTIONS.
WARNING: For emergency use only when administered by properly trained personnel for oxygen deficiency and resuscitation. For all other medical applications, Rx only.
CAUTION: Federal law prohibits dispensing without prescription. Uninterrupted use of high concentrations of oxygen over a long duration, without monitoring its effect on oxygen content of arterial blood, may be harmful. Use only with pressure reducing equipment and apparatus designed for oxygen. Do not attempt to use on patients who have stopped breathing, unless used in conjunction with resuscitative equipment. Produced by Air Liquefaction.
WARNING: EXTREMELY COLD, OXIDIZING LIQUID AND GAS UNDER PRESSURE. VIGOROUSLY ACCELERATES COMBUSTION. COMBUSTIBLES IN CONTACT WITH LIQUID OXYGEN MAY EXPLODE ON IGNITION OR IMPACT. CAN CAUSE SEVERE FROSTBITE. Keep oil, grease, and combustibles away. Use only with equipment cleaned for oxygen. Store and use with adequate ventilation. Do not get liquid in eyes, on skin, or clothing. For liquid withdrawal, wear face shield and gloves. Do not drop. Use suitable hand truck for container movement. Avoid spills. Do not walk on or roll equipment over spills. Cylinder temperature should not exceed 52C (125F). Close valve after each use and when empty. Use back flow preventive device in the piping. Use in accordance with the Material Safety Data Sheets (MSDS). FIRST AID: IN CASE OF FROSTBITE, obtain medical treatment immediately. CAS: 7782-44-7 DO NOT REMOVE THIS PRODUCT LABEL.
AIRGAS PURITAN MEDICAL Airgas Intermountain, Inc. Denver, CO 80216 (303) 370-7800
841533 (10/04)

PACKAGE LABEL

OXYGEN, REFRIGERATED LIQUID USP UN1073 OXYGEN 2
ALWAYS KEEP CONTAINER IN UPRIGHT POSITION
WARNING: For emergency use only when administered by properly trained personnel for oxygen deficiency and resuscitation. For all other medical applications, Rx only.
CAUTION: Federal law prohibits dispensing without prescription. Uninterrupted use of high concentrations of oxygen over a long duration, without monitoring its effect on oxygen content of arterial blood, may be harmful. Use only with pressure reducing equipment and apparatus designed for oxygen. Do not attempt to use on patients who have stopped breathing, unless used in conjunction with resuscitative equipment. Produced by Air Liquefaction.
WARNING: EXTREMELY COLD, OXIDIZING LIQUID AND GAS UNDER PRESSURE. VIGOROUSLY ACCELERATES COMBUSTION. COMBUSTIBLES IN CONTACT WITH LIQUID OXYGEN MAY EXPLODE ON IGNITION OR IMPACT. CAN CAUSE SEVERE FROSTBITE. Keep oil, grease, and combustibles away. Use only with equipment cleaned for oxygen. Store and use with adequate ventilation. Do not get liquid in eyes, on skin, or clothing. For liquid withdrawal, wear face shield and gloves. Do not drop. Use suitable hand truck for container movement. Avoid spills. Do not walk on or roll equipment over spills. Cylinder temperature should not exceed 52C (125F). Close valve after each use and when empty. Use in accordance with the Material Safety Data Sheets (MSDS). FIRST AID: IN CASE OF FROSTBITE, obtain medical treatment immediately. CAS: 7782-44-7 DO NOT REMOVE THIS PRODUCT LABEL.
AIRGAS PURITAN MEDICAL Airgas Intermountain, Inc. Denver, CO 80216 (303) 370-7800
40136 (04/02)